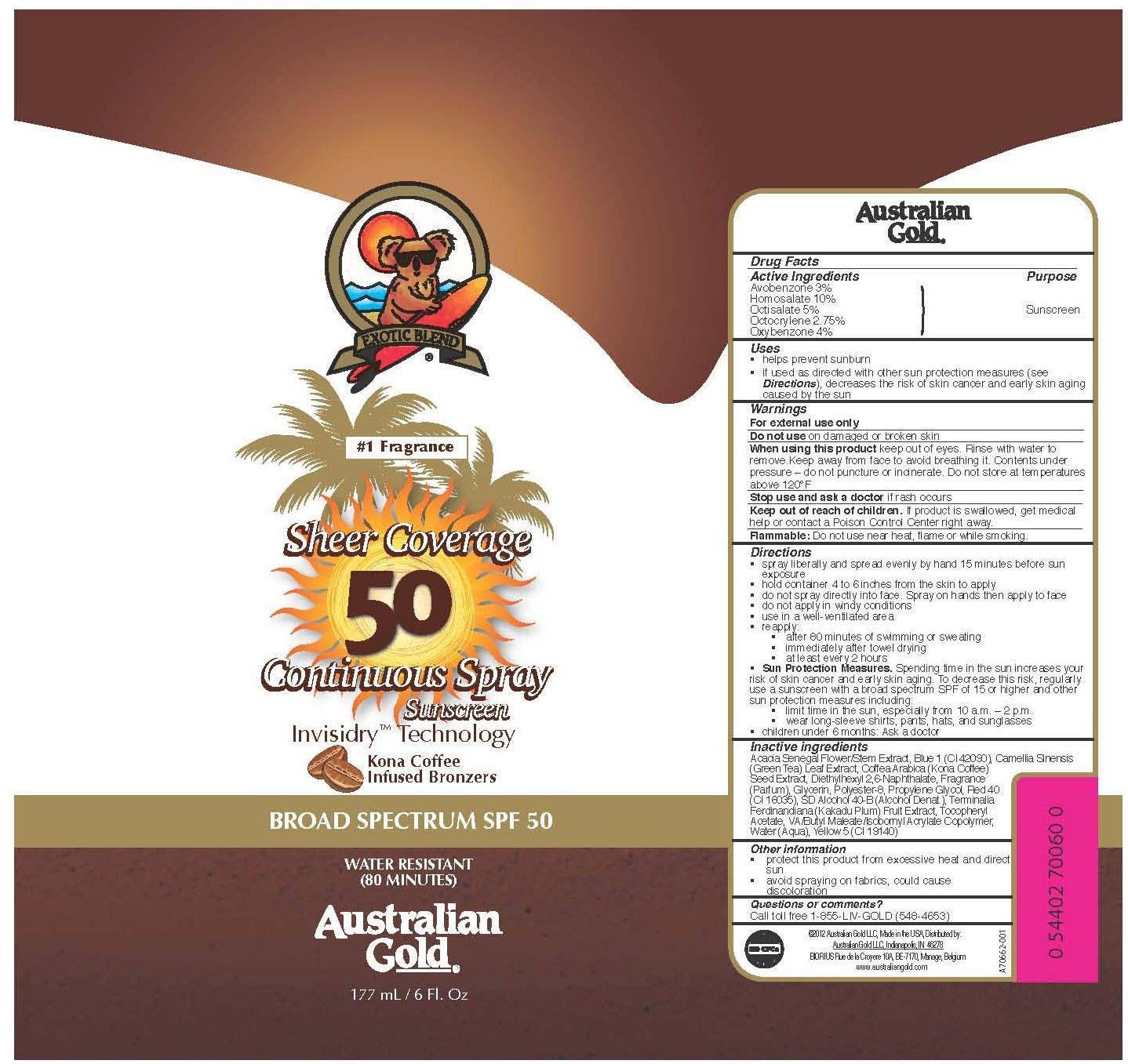 DRUG LABEL: Australian Gold
NDC: 13630-0027 | Form: SPRAY
Manufacturer: Prime Packaging, Inc.
Category: otc | Type: HUMAN OTC DRUG LABEL
Date: 20200117

ACTIVE INGREDIENTS: AVOBENZONE 25.8 mg/1 mL; HOMOSALATE 86 mg/1 mL; OCTISALATE 43 mg/1 mL; OCTOCRYLENE 23.7 mg/1 mL; OXYBENZONE 34.4 mg/1 mL
INACTIVE INGREDIENTS: ALCOHOL; FD&C BLUE NO. 1; DIETHYLHEXYL 2,6-NAPHTHALATE; POLYESTER-8 (1400 MW, CYANODIPHENYLPROPENOYL CAPPED); FD&C RED NO. 40; .ALPHA.-TOCOPHEROL ACETATE; WATER; GLYCERIN; ACACIA SENEGAL FLOWER; PROPYLENE GLYCOL; GREEN TEA LEAF; ARABICA COFFEE BEAN; FD&C YELLOW NO. 5

Active ingredients

Avobenzone 3 %, Homosalate 10 %, Octisalate 5 %, Octocrylene 2.75 %, Oxybenzone 4 %

Purpose

Sunscreen

Uses

- helps prevent sunburn
- if used as directed with other sun protection measures (see Directions), decreases the risk of skin cancer and early skin aging caused by the sun

Warnings

OTHER SAFETY INFORMATION

For external use only

Do not use on damaged or broken skin.

When using this product keep out of eyes. Rinse with water to remove. Keep away from face to avoid breathing it. Contents under pressure - do not puncture or incinirate. Do not store at temperatures above 120^0F

Stop use and ask a doctor if rash occurs.

Keep out of reach of children. If product is swallowed, get medical help or contact a Poison Control Center right away.

OTHER SAFETY INFORMATION

Flammable: Do not use near heat, flame or while smoking

Directions

- spray liberally and spread evenly by hand 15 minutes before sun exposure
- hold container 4 to 6 inches from the skin to apply
- do not spray directly into face. Spray on hands then apply to face
- do not apply in windy conditions
- use in well ventilated area
- reapply:
  - after 80 minutes of swimming or sweating
  - immediately after towel drying
  - at least every 2 hours
- Sun Protection Measures. Spending time in the sun increases your risk of skin cancer and early skin aging. To decrease this risk, regularly use a sunscreen with broad spectrum SPF of 15 or higher and other sun protection measures including:
  - limit time in the sun, especially from 10 a.m. – 2 p.m.
  - wear long-sleeve shirts, pants, hats, and sunglasses
- Children under 6 months: Ask a doctor

Inactive Ingredients

Acacia Senegal Flower/Stem Extract, Blue 1 (CI 42090), Camellia Sinensis (Green Tea) Leaf Extract, Coffea Arabica (Kona Coffee) Seed Extract, Diethylhexyl 2,6-Naphthalate, Fragrance (Parfum), Glycerin, Polyester-8, Propylene Glycol, Red 40 (CI 16035), SD Alcohol 40-B (Alcohol Denat.), Terminalia Ferdinandiana (Kakadu Plum) Fruit Extract, Tocopheryl Aceate, VA/Butyl Maleate/Isobornyl Acrylate Copolymer, Water (Aqua), Yellow 5 (CI 19140)

Other information

- protect this product from excesive heat and direct sun
- avoid spraying on fabrics - could cause discoloration

Questions or Comments?

Call toll free 1-855-LIV-GOLD (548-4653)

PRINCIPAL DISPLAY PANEL - 177 mL Can Label

EXOTIC BLEND

#1 Fragrance

Sheer Coverage

50

Continuous Spray

Sunscreen

Invisidry Technology

Kona Coffee

Infused Bronzers

BROAD SPECTRUM SPF 50

WATER RESISANT

(80 MINUTES)

Australian Gold

177 mL / 6 Fl. Oz